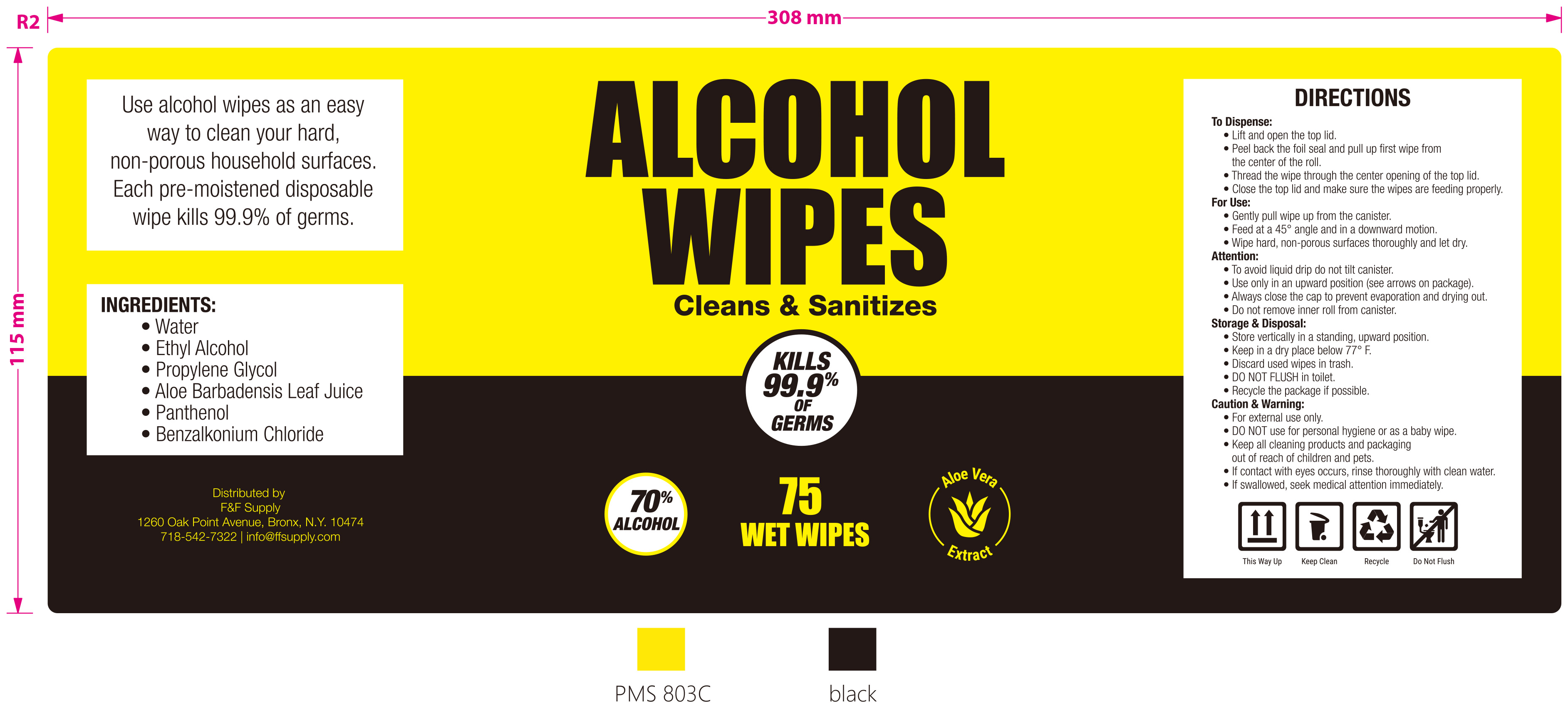 DRUG LABEL: Alcohol Wipes
NDC: 71766-005 | Form: SWAB
Manufacturer: Hangzhou Linkeweier Daily Chemicals Co. Ltd.
Category: otc | Type: HUMAN OTC DRUG LABEL
Date: 20210224

ACTIVE INGREDIENTS: ALCOHOL 70 1/100 1
INACTIVE INGREDIENTS: BENZALKONIUM CHLORIDE; PANTHENOL; PROPYLENE GLYCOL; WATER; ALOE VERA LEAF

F&F Wipe-Off Canister Wipes

ACTIVE INGREDIENT

Alcohol 70%

PURPOSE

Antiseptic

For Use

- Lift and open the top lid.
- Peel back the foil seal and pull up first wipe from the center of the roll.
- Thread the wipe through the center opening of the top lid.
- Close the top lid and make sure the wipes are feeding properly.
- Gently pull wipe up from the canister.
- Feed at a 45° angle and in a downward motion.
- Wipe hard, non-porous surface thoroughly and let dry.

Warning

For external use only.

DO NOT USE for personal hygiene or as a baby wipe.

Stop use and ask a doctor

If contact with eyes occurs, rinse thoroughly with clean water.

If swallowed. seek medical attention immediately.

Keep out of reach from children

Keep all cleaning products and packaging out of reach of children and pets.

Attention

- To avoid liquid drip do not tilt canister.
- Use only in an upward position (see arrows on package).
- Always close the cap to prevent evaporation and drying out.
- Do not remove inner roll from canister.

Storage & Disposal

Store vertically in a standing,upward position.

Keep in a dry place below 77°F.

Discard used wipes in trash.

Do not flush in toilet.

Recycle the package if possible.

INACTIVE INGREDIENT

Water, Propylene Glycol, Aloe Barbadensis Leaf Juice, Panthenol, Benzalkonium Chloride

PACKAGE LABEL

75 IN A CANISTER NDC: 71766-005-01